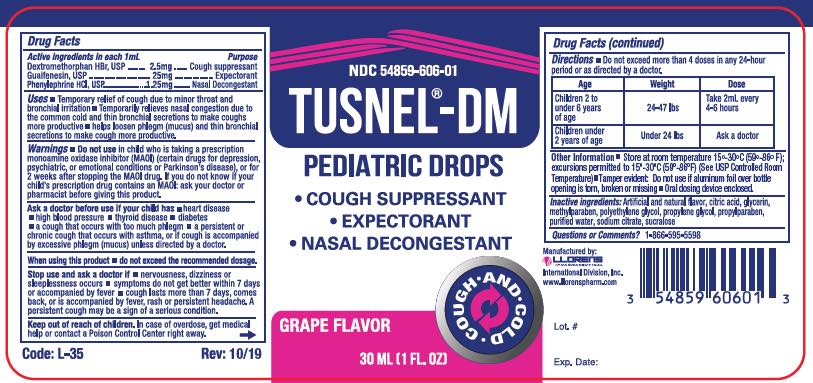 DRUG LABEL: Tusnel-DM Pediatric
NDC: 54859-606 | Form: SOLUTION/ DROPS
Manufacturer: LLORENS PHARMACEUTICALS INTERNATIONAL DIVISION
Category: otc | Type: HUMAN OTC DRUG LABEL
Date: 20251231

ACTIVE INGREDIENTS: DEXTROMETHORPHAN HYDROBROMIDE 2.5 mg/1 mL; GUAIFENESIN 25 mg/1 mL; PHENYLEPHRINE HYDROCHLORIDE 1.25 mg/1 mL
INACTIVE INGREDIENTS: ANHYDROUS CITRIC ACID; GLYCERIN; METHYLPARABEN; POLYETHYLENE GLYCOL, UNSPECIFIED; PROPYLENE GLYCOL; PROPYLPARABEN; WATER; SODIUM CITRATE; SUCRALOSE

Llorens-Tusnel DM Ped Dr 606

Active Ingredients in each (1 mL)

Dextromethorphan HBr 2.5 mg

Guaifenesin 25 mg

Phenylephrine HCl 1.25 mg

Purpose

Cough suppressant

Expectorant

Nasal Decongestant

Uses

- Temporary relief of cough due to minor throat and bronchial irritation
- Temporarily relieves nasal congestion due to the common cold and thin bronchial secretions to make coughs more productive
- Helps loosen phlegm (mucus) and thin bronchial secretions to make cough more productive.

Warnings

Do not use in child whos is taking a prescription monoamine oxidase inhibitor (MAOI) (certain drugs for depression, psychiatric, or emotional conditions or Parkinson's disease), or for 2 weeks after stopping the MAOI drug. If you do not know if your child's prescription drug contains an MAOI: ask your doctor or pharmacist before giving this product.

Ask a doctor before use if your child has

- heart disease
- high blood pressure
- thyroid disease
- diabetes
- a cough that occurs with too much phlegm
- a persistent or chronic cough that occurs with asthma, or if cough is accompanied by excessive phlegm (mucus) unless directed by a doctor.

When using this product

- do not exceed the recommended dosage.

Stope use and ask doctor if

- nervousness, dizziness or sleeplessness occurs
- symptoms do not get better within 7 days or accompanied by fever
- cough lasts more than 7 days, comes back, or is accompanied by fever, rash or persistent headache. A persistent cough may be a sign of a serious condition.

Keep out of reach of children. In case overdose, get medical help or contact a Poison Control Center right away.

Directions

Do not exceed more than 4 doses in any 24-hour period or as directed by a doctor.

Age | Weight | Dose
Children 2 to under 6 years of age | 24-47 lbs | Take 2 mL every 4-6 hours
Children under 2 years of age | Under 24 lbs | Ask a doctor

INACTIVE INGREDIENT

Inactive ingredients: Artifical and natural flavor, citric acid, glycerin, methylparaben, polyethylene glycol, propylene glycol, propylparaben, purified water, sodium citrate, sucralose.

Questions or Comments? 1-866-595-5598